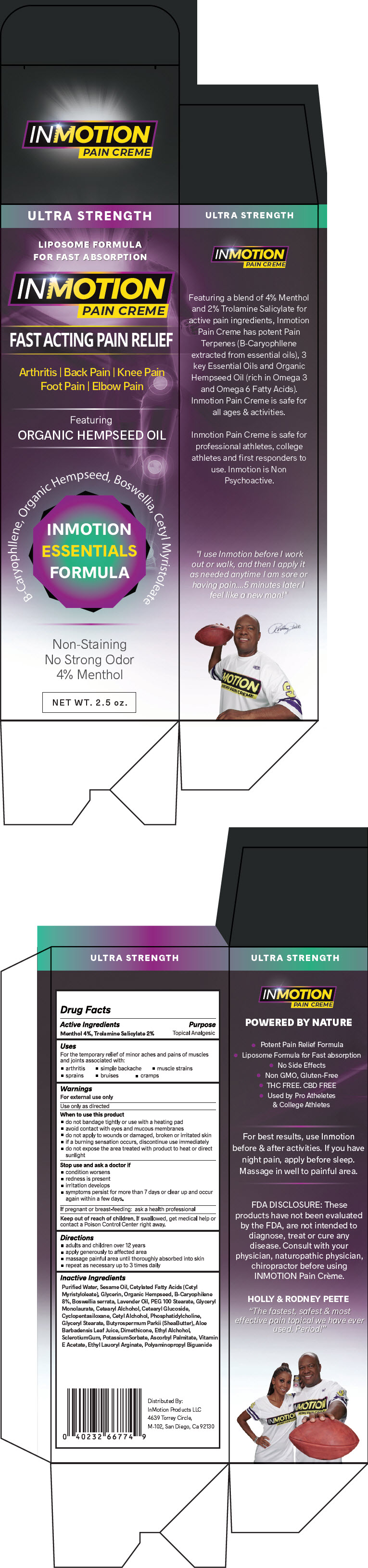 DRUG LABEL: Inmotion Pain Creme Ultra Strength
NDC: 72581-428 | Form: CREAM
Manufacturer: Inmotion Products LLC
Category: otc | Type: HUMAN OTC DRUG LABEL
Date: 20190515

ACTIVE INGREDIENTS: Menthol, Unspecified Form 40 mg/1 mL; Trolamine Salicylate 20 mg/1 mL
INACTIVE INGREDIENTS: Water; Sesame Oil; Cetyl Myristoleate; Glycerin; Indian Frankincense; Lavender Oil; Peg-100 Stearate; Glyceryl Laurate; Cetostearyl Alcohol; Cetearyl Glucoside; Cyclomethicone 5; Cetyl Alcohol; Glyceryl Monostearate; Shea Butter; Aloe Vera Leaf; Dimethicone; Alcohol; Betasizofiran; Potassium Sorbate; Ascorbyl Palmitate; .Alpha.-Tocopherol Acetate; Ethyl Lauroyl Arginate

Inmotion Pain Creme Ultra Strength

Drug Facts

Active Ingredients

Menthol 4%, Trolamine Salicylate 2%

Purpose

Topical Analgesic

Uses

For the temporary relief of minor aches and pains of muscles and joints associated with:

- arthritis
- simple backache
- muscle strains
- sprains
- bruises
- cramps

Warnings

For external use only

Use only as directed

When to use this product

- do not bandage tightly or use with a heating pad
- avoid contact with eyes and mucous membranes
- do not apply to wounds or damaged, broken or irritated skin
- if a burning sensation occurs, discontinue use immediately
- do not expose the area treated with product to heat or direct sunlight

Stop use and ask a doctor if

- condition worsens
- redness is present
- irritation develops
- symptoms persist for more than 7 days or clear up and occur again within a few days.

PREGNANCY OR BREAST FEEDING

If pregnant or breast-feeding: ask a health professional

Keep out of reach of children. If swallowed, get medical help or contact a Poison Control Center right away.

Directions

- adults and children over 12 years
- apply generously to affected area
- massage painful area until thoroughly absorbed into skin
- repeat as necessary up to 3 times daily

Inactive Ingredients

Purified Water, Sesame Oil, Cetylated Fatty Acids (Cetyl Myristyloleate), Glycerin, Organic Hempseed, B-Caryophilene 8%, Boswellia serrata, Lavender Oil, PEG 100 Stearate, Glyceryl Monolaurate, Cetearyl Alchohol, Cetearyl Glucoside, Cyclopentasiloxane, Cetyl Alchohol, Phosphatidylcholine, Glyceryl Stearate, Butyrospermum Parkii (SheaButter), Aloe Barbadensis Leaf Juice, Dimethicone, Ethyl Alchohol, SclerotiumGum, PotassiumSorbate, Ascorbyl Palmitate, Vitamin E Acetate, Ethyl Lauoryl Arginate, Polyaminopropyl Biguanide

Distributed By:
InMotion Products LLC
4639 Torrey Circle,
M-102, San Diego, Ca 92130

PRINCIPAL DISPLAY PANEL - 2.5 oz Tube Carton

ULTRA STRENGTH

LIPOSOME FORMULA
FOR FAST ABSORPTION

INMOTION
PAIN CREME

FAST ACTING PAIN RELIEF

Arthritis | Back Pain | Knee Pain
Foot Pain | Elbow Pain

Featuring
ORGANIC HEMPSEED OIL

B-Caryophllene, Organic Hempseed, Boswellia, Cetyl Myristoleate

INMOTION
ESSENTIALS
FORMULA

Non-Staining
No Strong Odor
4% Menthol

NET WT. 2.5 oz.